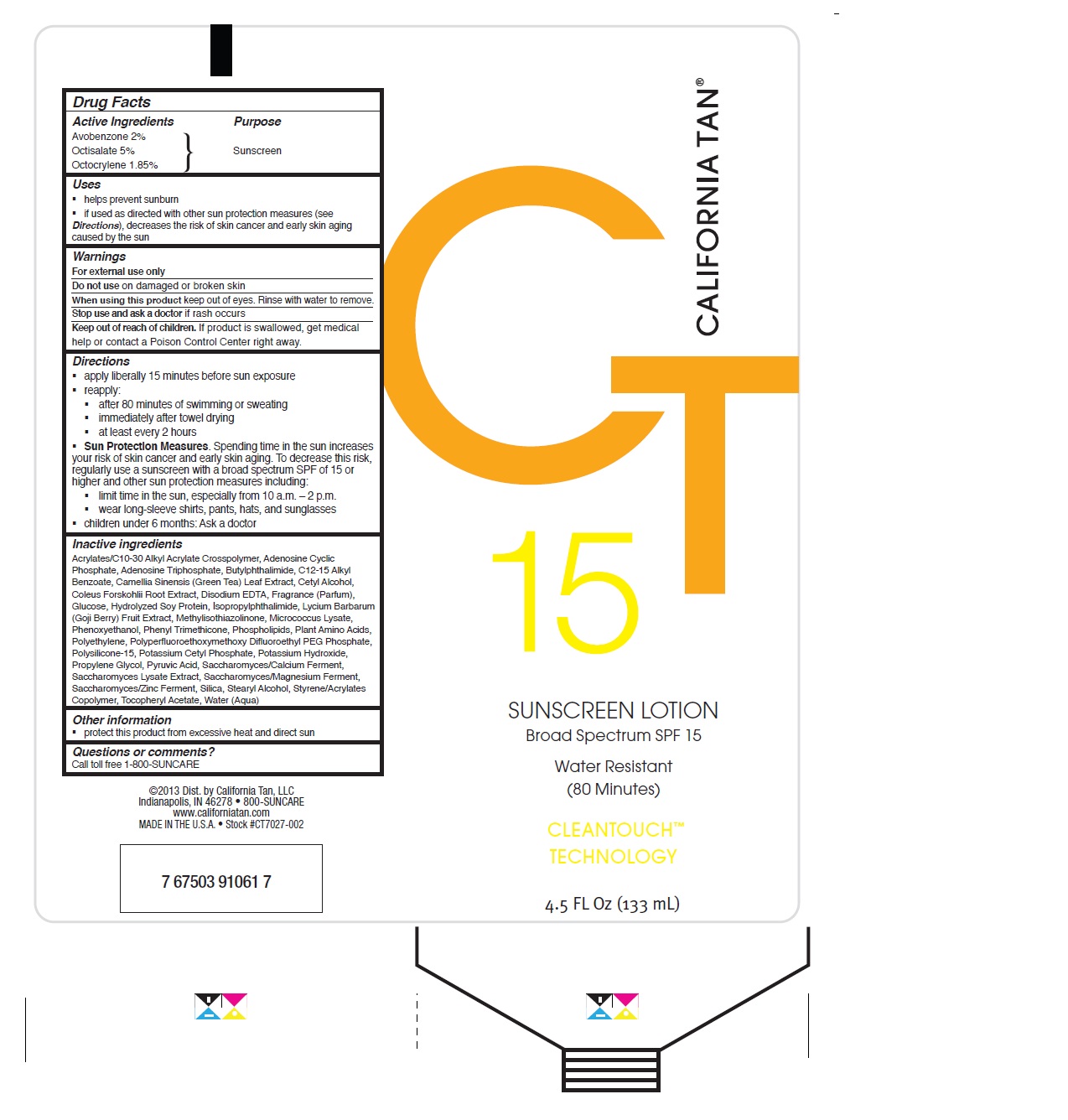 DRUG LABEL: California Tan
NDC: 58443-0169 | Form: LOTION
Manufacturer: Prime Enterprises Inc.
Category: otc | Type: HUMAN OTC DRUG LABEL
Date: 20200117

ACTIVE INGREDIENTS: AVOBENZONE 20 mg/1 mL; OCTISALATE 50 mg/1 mL; OCTOCRYLENE 18.5 mg/1 mL
INACTIVE INGREDIENTS: STEARYL ALCOHOL; STYRENE/ACRYLAMIDE COPOLYMER (MW 500000); SACCHAROMYCES CEREVISIAE; SILICON DIOXIDE; SACCHAROMYCES LYSATE; POTASSIUM HYDROXIDE; PYRUVIC ACID; AMINO ACIDS; EDETATE DISODIUM; PHENYL TRIMETHICONE; MICROCOCCUS LUTEUS; LYCIUM BARBARUM FRUIT; ADENOSINE CYCLIC PHOSPHATE; ADENOSINE TRIPHOSPHATE; PHENOXYETHANOL; HIGH DENSITY POLYETHYLENE; POLYSILICONE-15; POTASSIUM CETYL PHOSPHATE; PROPYLENE GLYCOL; DEXTROSE; (C10-C30)ALKYL METHACRYLATE ESTER; GREEN TEA LEAF; CETYL ALCOHOL; N-BUTYLPHTHALIMIDE; COLEUS FORSKOHLII ROOT OIL; SOY PROTEIN; ALPHA-TOCOPHEROL ACETATE; ISOPROPYLPHTHALIMIDE; WATER; METHYLISOTHIAZOLINONE; LECITHIN, SOYBEAN; ALKYL (C12-15) BENZOATE

California Tan SPF 15 Sunscreen

Active Ingredients

Avobenzone 2%

Octisalate 5%

Octocrylene 1.85%

PURPOSE

Sunscreen

Uses

- helps prevent sunburn
- if used as directed with other sun protection measures (see Directions), decreases the risk of skin cancer and early skin aging caused by the sun

WARNINGS

For external use only.

Do not use on damaged or broken skin

When using this product keep out of eyes. Rinse with water to remove.

Stop use and ask a doctor if rash occurs

Keep out of reach of children. If product is swallowed, get medical help or contact a Poison Control Center right away.

Directions

- apply liberally 15 minutes before sun exposure
- reapply:
- after 80 minutes of swimming or sweating
- immediately after towel drying
- at least every 2 hours
- Sun Protection Measures. Spending time in the sun increases your risk of skin cancer and early skin aging. To decrease this risk, regularly use a sunscreen with broad spectrum SPF of 15 or higher and other sun protection measures including:
- limit time in the sun, especially from 10 a.m. – 2 p.m.
- wear long-sleeve shirts, pants, hats, and sunglasses
- children under 6 months: Ask a doctor

INACTIVE INGREDIENT

Acrylates/C10-30 Alkyl Acrylate Crosspolymer, Adenosine Cyclic Phosphate, Adenosine Triphosphate, Butylphthalimide, C12-15 Alkyl Benzoate, Camellia Sinensis (Green Tea) Leaf Extract, Cetyl Alcohol, Coleus Forskohlii Root Extract, Disodium EDTA, Fragrance (Parfum), Glucose, Hydrolyzed Soy Protein, Isopropylphthalimide, Lycium Barbarum (Goji Berry) Fruit Extract, Methylisothiazolinone, Micrococcus Lysate, Phenoxyethanol, Phenyl Trimethicone, Phospholipids, Plant Amino Acids, Polyethylene, Polyperfluoroethoxymethoxy Difluoroethyl PEG Phosphate, Polysilicone-15, Potassium Cetyl Phosphate, Potassium Hydroxide, Propylene Glycol, Pyruvic Acid, Saccharomyces/Calcium Ferment, Saccharomyces Lysate Extract, Saccharomyces/Magnesium Ferment, Saccharomyces/Zinc Ferment, Silica, Stearyl Alcohol, Styrene/Acrylates Copolymer, Tocopheryl Acetate, Water (Aqua)

Other Information

- protect this product from excesive heat and direct sun

Questions or Comments?

Call toll free 1-800-SUNCARE